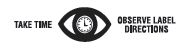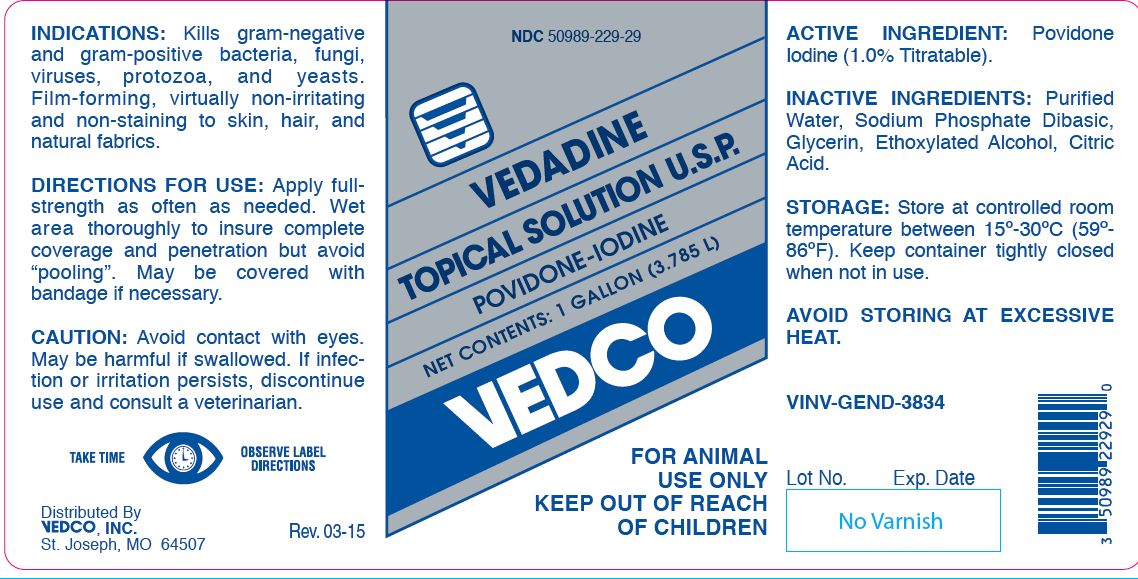 DRUG LABEL: VEDADINE TOPICAL
NDC: 50989-229 | Form: SOLUTION
Manufacturer: Vedco, Inc.
Category: animal | Type: OTC ANIMAL DRUG LABEL
Date: 20221116

ACTIVE INGREDIENTS: POVIDONE-IODINE 65.9 g/1 L

VEDADINE TOPICAL SOLUTION
POVIDONE-IODINE

KEEP OUT OF REACH OF CHILDREN

FOR ANIMAL USE ONLY
KEEP OUT OF REACH OF CHILDREN

INDICATIONS:

Kills gram-negative and gram-positive bacteria, fungi, viruses, protozoa, and yeasts. Film-forming, virtually non-irritating and non-staining to skin, hair, and natural fabrics.

DIRECTIONS FOR USE:

Apply fullstrength as often as needed. Wet area thoroughly to insure complete coverage and penetration but avoid “pooling”. May be covered with bandage if necessary.

CAUTION:

Avoid contact with eyes. May be harmful if swallowed. If infection or irritation persists, discontinue use and consult a veterinarian.

ACTIVE INGREDIENT:

Povidone Iodine (1.0% Titratable).

INACTIVE INGREDIENTS:

Purified Water, Sodium Phosphate Dibasic, Glycerin, Ethoxylated Alcohol, Citric Acid.

STORAGE:

Store at controlled room temperature between 15º-30ºC (59º- 86ºF). Keep container tightly closed when not in use.

AVOID STORING AT EXCESSIVE HEAT.

NET CONTENTS:

1 GALLON (3.785 L) VINV-GEND-3834

INFORMATION FOR OWNERS/CAREGIVERS

Distributed By
VEDCO, INC.
St. Joseph, MO 64507